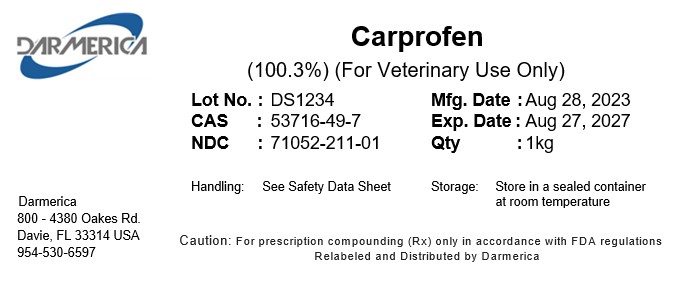 DRUG LABEL: Carprofen
NDC: 71052-211 | Form: POWDER
Manufacturer: DARMERICA, LLC
Category: other | Type: BULK INGREDIENT - ANIMAL DRUG
Date: 20241219

ACTIVE INGREDIENTS: Carprofen 1 kg/1 kg

Carprofen